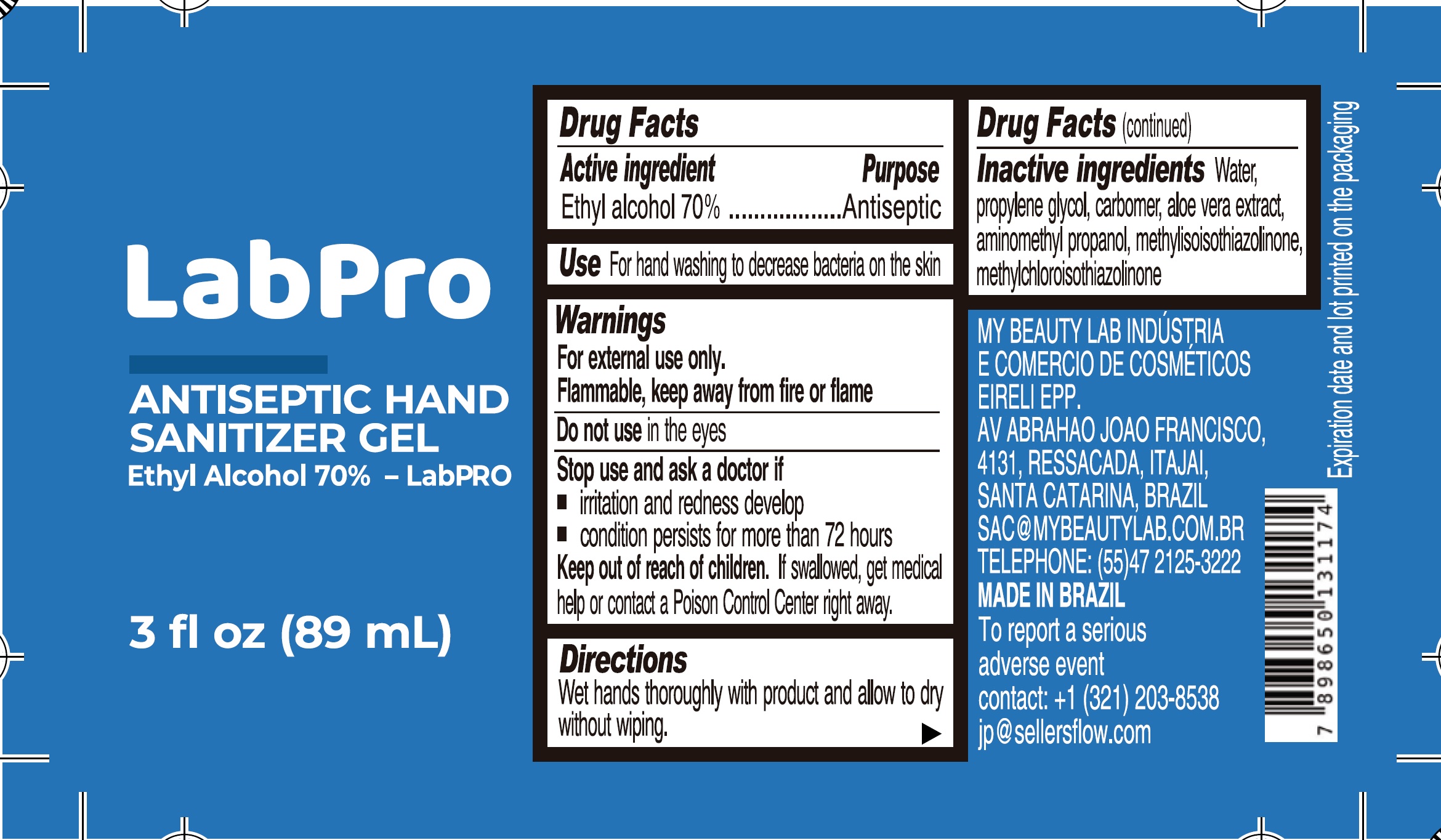 DRUG LABEL: LabPro Antiseptic Hand Sanitizer
NDC: 81223-000 | Form: GEL
Manufacturer: MY BEAUTY LAB INDUSTRIA E COMERCIO DE COSMETICOS EIRELI
Category: otc | Type: HUMAN OTC DRUG LABEL
Date: 20201218

ACTIVE INGREDIENTS: ALCOHOL 0.7 mL/1 mL
INACTIVE INGREDIENTS: WATER; PROPYLENE GLYCOL; CARBOMER HOMOPOLYMER, UNSPECIFIED TYPE; ALOE VERA LEAF; AMINOMETHYLPROPANOL; METHYLISOTHIAZOLINONE; METHYLCHLOROISOTHIAZOLINONE

LabPro Antiseptic Hand Sanitizer Gel

Active ingredient

Ethyl alcohol 70%

Purpose

Antiseptic

Use

For hand washing to decrease bacteria on the skin

Warnings

For external use only.
Flammable. keep away from fire or flame

Do not use

in the eyes

Stop use and ask a doctor if

- irrtation or redness develop
- conditions persist for more than 72 hours

Keep out of reach of children.

If swallowed, get medical help or contact a Poison Control Center right away.

Direction

Wet hands thoroughly with product and allow to dry without wiping.

Inactive ingredients

Water, propylene glycol, carbomer, aloe vera extract, propylene glycol, carbomer, aloe vera extract, amonimethyl propanol, methylisoisothiszolinone, methylchloroisothiazolinone